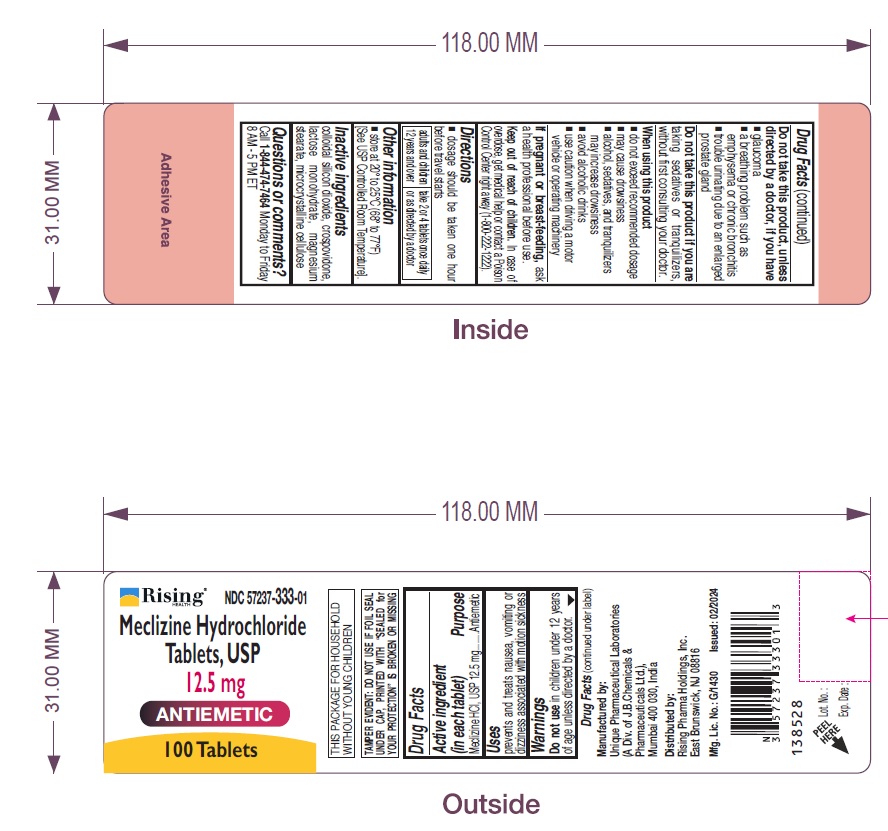 DRUG LABEL: Meclizine HCl
NDC: 57237-333 | Form: TABLET
Manufacturer: Rising Pharma Holdings, Inc.
Category: otc | Type: HUMAN OTC DRUG LABEL
Date: 20241113

ACTIVE INGREDIENTS: MECLIZINE HYDROCHLORIDE 12.5 mg/1 1
INACTIVE INGREDIENTS: SILICON DIOXIDE; CROSPOVIDONE; LACTOSE MONOHYDRATE; MAGNESIUM STEARATE; MICROCRYSTALLINE CELLULOSE

MECLIZINE HYDROCHLORIDE TABLETS, USP 12.5 mg

Drug Facts Active ingredient (in each tablet)

Meclizine HCl, USP 12.5 mg

Purpose

Antiemetic

Uses

prevents and treats nausea, vomiting or dizziness associated with motion sickness.

Warnings

Do not use in children under 12 years of age unless directed by a doctor.

WARNINGS

Do not take this product, unless directed by a doctor, if you have

- glaucoma
- a breathing problem such as emphysema or chronic bronchitis
- trouble urinating due to an enlarged prostate gland

WARNINGS

Do not take this product if you are

taking sedatives or tranquilizers, without first consulting your doctor.

When using this product

- do not exceed recommended dosage
- may cause drowsiness
- alcohol, sedatives, and tranquilizers may increase drowsiness
- avoid alcoholic drinks
- use caution when driving a motor vehicle or operating machinery

PREGNANCY OR BREAST FEEDING

If pregnant or breast-feeding, ask a health professional before use.

Keep out of reach of children. In case of overdose, get medical help or contact a Poison Control Center right away (1-800-222-1222).

Directions

dosage should be taken one hour before travel starts

adults and children 12 years and over | take 2 or 4 tablets once daily or as directed by a doctor

Other information

- store at 20° to 25°C (68° to 77°F) [See USP Controlled Room Temperature].

Inactive ingredients

colloidal silicon dioxide, crospovidone, lactose monohydrate, magnesium stearate, microcrystalline cellulose

Questions or comments?

Call 1-844-474-7464 Monday to Friday 8 AM - 5 PM ET

Manufactured by:
Unique Pharmaceutical Laboratories
(A Div. of J.B.Chemicals &
Pharmaceuticals Ltd.),
Mumbai 400 030, India

Mfg. Lic. No.: G/1430

Distributed by:
Rising Pharma Holdings, Inc.
East Brunswick, NJ 08816

Issued: 02/2024

138528

PRINCIPAL DISPLAY PANEL - 12.5 mg tablets container label

NDC 57237-333-01

Meclizine Hydrochloride Tablets, USP
12.5 mg

100 Tablets